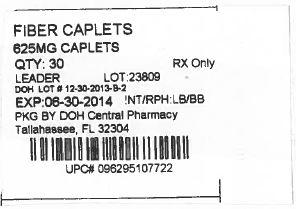 DRUG LABEL: Leader Fiber
NDC: 53808-0963 | Form: TABLET, FILM COATED
Manufacturer: State of Florida DOH Central Pharmacy
Category: otc | Type: HUMAN OTC DRUG LABEL
Date: 20140303

ACTIVE INGREDIENTS: CALCIUM POLYCARBOPHIL 625 mg/1 1
INACTIVE INGREDIENTS: CALCIUM CARBONATE; CARAMEL; CROSPOVIDONE; HYPROMELLOSE 2208 (100 MPA.S); MALTODEXTRIN; CELLULOSE, MICROCRYSTALLINE; MAGNESIUM STEARATE; POLYETHYLENE GLYCOL 200; COLLOIDAL SILICON DIOXIDE; SODIUM LAURYL SULFATE

Leader Fiber Caplets Drug Facts

Active ingredient (in each caplet)

Calcium polycarbophil 625 mg

Purpose

Bulk-forming laxative

Uses

relieves:

- constipation
- helps restore & maintain regularity
- promotes normal function of the bowel

Warnings

Do not use if

- you have abdominal pain, nausea or vomiting
- you have difficulty in swallowing
- you have noticed a sudden change in bowel habits that persists over a period of 2 weeks

Taking this product without adequate fluid may cause it to swell and block your throat or esophagus and may cause choking.

Stop use and ask a doctor if

- you experience chest pain, abdominal pain, nausea, vomiting, difficulty in breathing or swallowing
- you fail to have a bowel movement after use
- rectal bleeding occurs
- symptoms persist more than 1 week

Drug interaction precaution: Contains calcium. If you are taking any form of tetracycline antibiotic, this product should be taken 1 hour before or 2 hours after you have taken the antibiotic

Keep out of reach of children.

In case of overdose, get medical help or contact a Poison Control Center right away.

Directions

- take this product (child or adult dose) with a full glass of water (8oz)
- daily maximum 4 doses
- dosage may vary according to diet, exercise, previous laxative use or severity of constipation
- continued use for 1 to 3 days is normally required to provide full benefit
-
  adults and children 12 years of age and over | 2 caplets once a day | up to 4 times a day
  children under 12 years | consult a physician

Other information

- each caplet contains: calcium 122 mg
- do not use if printed seal under cap is torn or missing
- store at room temperature
- protect contents from moisture

Inactive ingredients

calcium carbonate, caramel, crospovidone, hypromellose, maltodextrin, microcrystalline cellulose, magnesium stearate, methylcellulose, polyethylene glycol, silicon dioxide, sodium lauryl sulfate

PACKAGE LABEL

Distributed By:

Cardinal Health

Dublin Ohio 43017

www.myleader.com

This Product was Repackaged By:

State of Florida DOH Central Pharmacy
104-2 Hamilton Park Drive
Tallahassee, FL 32304
USA

Label Image for 53808-0963
625mg